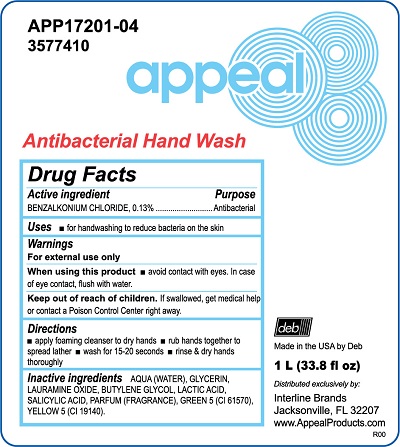 DRUG LABEL: Appeal Antibacterial Hand Wash
NDC: 11084-015 | Form: SOLUTION
Manufacturer: SC Johnson Professional USA, Inc.
Category: otc | Type: HUMAN OTC DRUG LABEL
Date: 20241216

ACTIVE INGREDIENTS: BENZALKONIUM CHLORIDE 0.13 g/100 mL
INACTIVE INGREDIENTS: WATER; GLYCERIN; LAURAMINE OXIDE; BUTYLENE GLYCOL; LACTIC ACID, UNSPECIFIED FORM; SALICYLIC ACID; D&C GREEN NO. 5; FD&C YELLOW NO. 5

Drug Facts

Active ingredient

BENZALKONIUM CHLORIDE, 0.13%

Purpose

Antibacterial

Uses

for handwashing to reduce bacteria on the skin

Warnings

When using this product

avoid contact with eyes. In case of eye contact, flush with water.

Keep out of reach of children.

If swallowed, get medical help or contact a Poison Control Center right away.

Directions

apply foaming cleanser to dry hands
rub hands together to spread lather
wash for 15-20 seconds
rinse & dry hands thoroughly

Inactive ingredients

AQUA (WATER), GLYCERIN, LAURAMINE OXIDE, BUTYLENE GLYCOL, LACTIC ACID, SALICYLIC ACID, PARFUM (FRAGRANCE), GREEN 5 (CI 61570), YELLOW 5 (CI 19140).

PACKAGE LABEL

APP17201-04

3577410

appeal

Antibacterial Hand Wash

deb

Made in the USA by Deb

1 L (33.8 fl oz)

Distributed exclusively by:

Interline Brands

Jacksonville, FL 32207

www.AppealProducts.com

R00